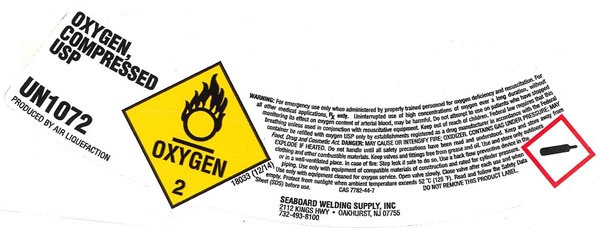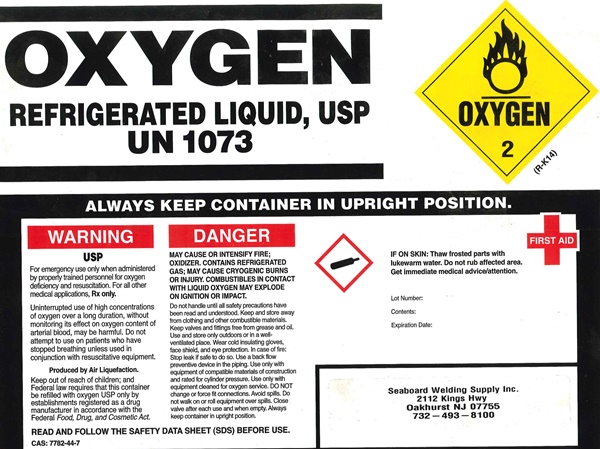 DRUG LABEL: OXYGEN
NDC: 42139-001 | Form: GAS
Manufacturer: Seaboard Welding Supply, Inc.
Category: prescription | Type: HUMAN PRESCRIPTION DRUG LABEL
Date: 20241028

ACTIVE INGREDIENTS: OXYGEN 99 L/100 L

Oxygen

OXYGEN COMPRESSED USP label

OXYGEN COMPRESSED USP

UN 1072

PRODUCED BY AIR LIQUEFACTION

OXYGEN-2 PRODUCED BY AIR LIQUEFACTION

18033 (12/14)

WARNING:For emergency use only when administered by properly trained personnel for oxygen deficiency and resuscitation. For all other medical applications, Rx only. Uninterrupted use of high concentrations of oxygen over a long duration, without monitoring its effect on oxygen content of arterial blood, may be harmful. Do not attempt to use on patients who have stopped breathing unless used in conjunction with resuscitative equipment. Keep out of reach of children. Federal law requires that this container be refilled with oxygen USP only by establishments registered as a drug manufacture in accordance with the Federal Food, Drug, and Cosmetic Act. DANGER: MAY CAUSE OR INTENSIFY FIRE; OXIDIZER. CONTAINS GAS UNDER PRESSURE; MAY EXPLODE IF HEATED. Do not handle until all safety precautions have been read and understood. Keep and store away from clothing and other combustible materials. Keep valves and fittings free from grease and oil. Use and store only outdoors or in a well-ventilated place. In case of fire: Stop leak if safe to do so. Use a back flow preventive device in the piping. use only with equipment of compatible materials of construction and rated for cylinder pressure. Use only with equipment cleaned for oxygen service. open valve slowly. Close valve after each use and when empty. protect from sunlight when ambient temperature exceeds 52°C (125°F). read and follow the Safety Data Sheet (SDS) before use

CAS 7782-44-7 DO NOT REMOVE THIS PRODUCT LABEL

SEABOARD WELDING SUPPLY, INC.

2112 KINGS HWY • OAKHURST, NJ 07755

732-493-8100

OXYGEN REFRIGERATED LIQUID, USP label

OXYGEN REFRIGERATED LIQUID, USP

UN 1073

OXYGEN 2

(R-K14)

ALWAYS KEP CONTAINER IN UPRIGHT POSITION.

WARNING

USP

For emergency use only when administered by properly trained personnel for oxygen deficiency and resuscitation. For all other medical applications, Rx only.

Uninterrupted use of high concentrations of oxygen over a long duration, without monitoring its effect on oxygen content of arterial blood, may be harmful. Do not attempt to use on patients who have stopped breathing unless used in conjunction with resuscitative equipment.

Produced by Air Liquefaction

Keep out of reach of children; and Federal law requires that this container be refilled with oxygen USP only by establishments registered as a drug manufacture in accordance with the Federal Food, Drug, and Cosmetic Act.

DANGER

MAY CAUSE OR INTENSIFY FIRE; OXIDIZER. CONTAINS REFRIGERATED GAS; MAY CAUSE CRYOGENIC BURNS OR INJURY. COMBUSTIBLES IN CONTACT WITH LIQUID OXYGEN MAY EXPLODE ON IGNITION OR IMPACT.

Do not handle until all safety precautions have been read and understood. Keep and store away from clothing and other combustible materials. Keep valves and fittings free from grease and oil. Use and store only outdoors or in a well-ventilated place. Wear cold insulating gloves, face shield, and eye protection.In case of fire: Stop leak if safe to do so. Use a back flow preventive device in the piping. Use only with equipment of compatible materials of construction and rated for cylinder pressure. Use only with equipment cleaned for oxygen service. DO NOT change or forcr fit connections. Avoid spills. Do not walk or roll equipment over spills. Close valve after each use and when empty. Always kep container in upright position.

READ AND FOLLOW THE SAFETY DATA SHEET (SDS) BEFORE USE.

CAS 7782-44-7

FIRST AID

IF ON SKIN: Thaw frosted parts with lukewarm water. Do not rub affected area. Get immediate medical advice/attention.

Lot Number:

Contents:

Expiration Date:

SEABOARD WELDING SUPPLY, INC.

2112 KINGS HWY • OAKHURST, NJ 07755

732-493-8100